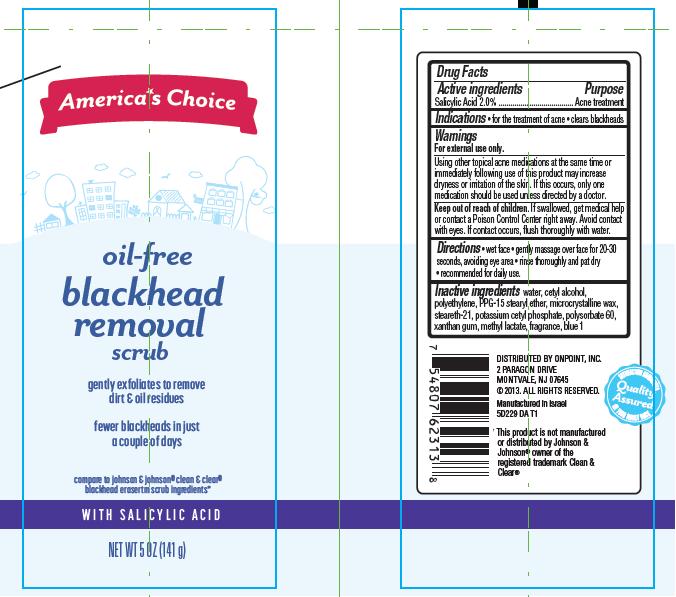 DRUG LABEL: Oil Free Blackhead Removal Scrub
NDC: 42421-229 | Form: CREAM
Manufacturer: Emilia Personal Care Inc.
Category: otc | Type: HUMAN OTC DRUG LABEL
Date: 20131112

ACTIVE INGREDIENTS: SALICYLIC ACID 2 g/100 g
INACTIVE INGREDIENTS: WATER; CETYL ALCOHOL; HIGH DENSITY POLYETHYLENE; PPG-15 STEARYL ETHER; MICROCRYSTALLINE WAX; STEARETH-21; POTASSIUM CETYL PHOSPHATE; POLYSORBATE 60; XANTHAN GUM; MENTHYL LACTATE, (-)-; FD&C BLUE NO. 1

America*s Choice Oil-Free Blackhead Removal

Active ingredient

Salicylic Acid 2.0%

Purpose

Acne Treatment

Indications

- for the treatment of acne
- clears backheads

Warnings

For external use only.

Using other topical acne medications at the same time or immediately following use of this product may increase dryness or irritation of the skin. If this occurs, only one medication should be used unless directed by a doctor.

Keep Out of Reach of Children.

If swallowed, get medical help or contact a Poison Control Center right away. Avoid contact with eyes. If contact occurs, flush thoroughly with water.

Directions

- wet face
- gently massage over face for 20-30 seconds, avoiding eye area
- rinse thoroughly and pat dry
- recommended for daily use.

Inactive ingredients

water, cetyl alcohol, polyethylene, PPG-15 stearyl ether, microcrystalline wax, steareth-21, potassium cetyl phosphate, polysorbate 60, xanthan gum, methyl lactate, fragrance, blue 1

Package/Label Principal Display Panel

America*s Choice
oil-free blackhead removal scrub

gently exfoliates to remove dirt & oil residues

fewer blackheads in just a couple of days

compare to johnson & johnson® clean & clear®
blackhead erasertm scrub ingredients

With Salicylic Acid

Net Wt 5 Oz (141 g)

Distributed by Onpoint, Inc.
2 Paragon Drive
Montvale, NJ 07645
©2013 All Rights Reserved.

Manufactured in Israel 5D229 DA T1

*This product is not manufactured or distributed by Johnson & Johnson® owner of the registered trademark Clean & Clear®

Label